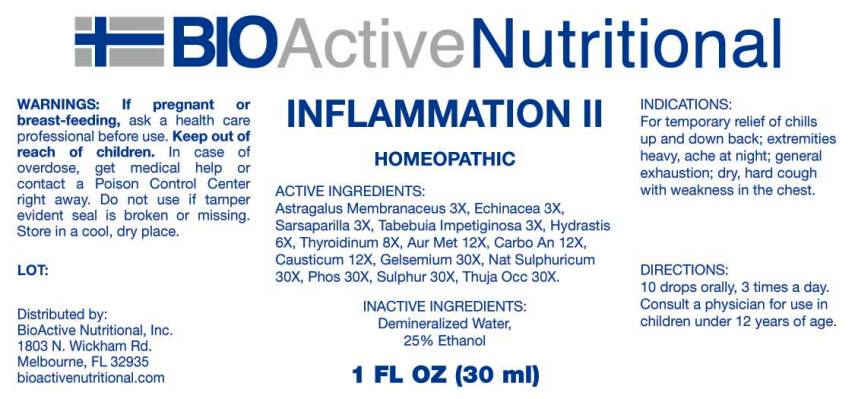 DRUG LABEL: Inflammation II
NDC: 43857-0418 | Form: LIQUID
Manufacturer: BioActive Nutritional, Inc.
Category: homeopathic | Type: HUMAN OTC DRUG LABEL
Date: 20161004

ACTIVE INGREDIENTS: ASTRAGALUS PROPINQUUS ROOT 3 [hp_X]/1 mL; ECHINACEA ANGUSTIFOLIA 3 [hp_X]/1 mL; SARSAPARILLA 3 [hp_X]/1 mL; TABEBUIA IMPETIGINOSA BARK 3 [hp_X]/1 mL; GOLDENSEAL 6 [hp_X]/1 mL; SUS SCROFA THYROID 8 [hp_X]/1 mL; GOLD 12 [hp_X]/1 mL; ACTIVATED CHARCOAL 12 [hp_X]/1 mL; CAUSTICUM 12 [hp_X]/1 mL; GELSEMIUM SEMPERVIRENS ROOT 30 [hp_X]/1 mL; SODIUM SULFATE 30 [hp_X]/1 mL; PHOSPHORUS 30 [hp_X]/1 mL; SULFUR 30 [hp_X]/1 mL; THUJA OCCIDENTALIS LEAFY TWIG 30 [hp_X]/1 mL
INACTIVE INGREDIENTS: WATER; ALCOHOL

Drug Facts:

ACTIVE INGREDIENTS:

Astragalus Membranaceus 3X, Echinacea (Angustifolia) 3X, Sarsaparilla (Smilax Regelii) 3X, Tabebuia Impetiginosa 3X, Hydrastis Canadensis 6X, Thyroidinum (Suis) 8X, Aurum Metallicum 12X, Carbo Animalis 12X, Causticum 12X, Gelsemium Sempervirens 30X, Natrum Sulphuricum 30X, Phosphorus 30X, Sulphur 30X, Thuja Occidentalis 30X.

INDICATIONS:

For temporary relief of chills up and down back; extremities heavy, ache at night; general exhaustion; dry, hard cough with weakness in the chest.

WARNINGS:

If pregnant or breast-feeding, ask a health care professional before use.

Keep out of reach of children. In case of overdose, get medical help or contact a Poison Control Center right away.

Do not use if tamper evident seal is broken or missing.

Store in cool, dry place.

Keep out of reach of children. In case of overdose, get medical help or contact a Poison Control Center right away.

DIRECTIONS:

10 drops orally, 3 times a day. Consult a physician for use in children under 12 years of age.

INDICATIONS:

For temporary relief of chills up and down back; extremities heavy, ache at night; general exhaustion; dry, hard cough with weakness in the chest.

INACTIVE INGREDIENTS:

Demineralized Water, 25% Ethanol

QUESTIONS:

Distributed by:
BioActive Nutritional, Inc.
1803 N. Wickham Rd.
Melbourne, FL 32935
bioactivenutritional.com

PACKAGE LABEL DISPLAY:

BIOActive Nutritional
INFLAMMATION II
HOMEOPATHIC
1 FL OZ (30 ml)